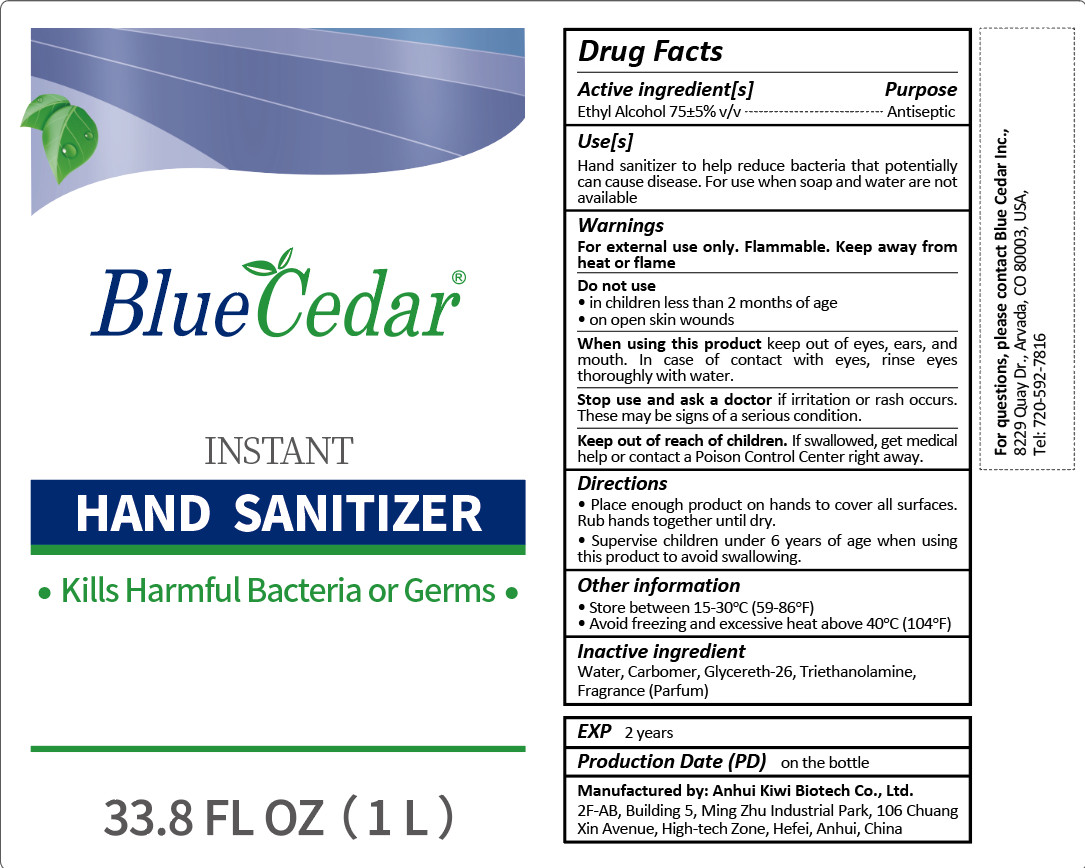 DRUG LABEL: Blue Cedar Hand Sanitizer
NDC: 55444-005 | Form: GEL
Manufacturer: Anhui Kiwi Biotech Co., Ltd.
Category: otc | Type: HUMAN OTC DRUG LABEL
Date: 20200622

ACTIVE INGREDIENTS: ALCOHOL 750 mL/1000 mL
INACTIVE INGREDIENTS: CARBOMER HOMOPOLYMER, UNSPECIFIED TYPE; TROLAMINE; GLYCERETH-26; FRAGRANCE LAVENDER & CHIA F-153480

DOSAGE AND ADMINISTRATION

1.Store between 15-30°C (59-86°F)
2.Avoid freezing and excessive heat above 40°C (104°F)

INACTIVE INGREDIENT

Water, Carbomer, Glycereth-26, Triethanolamine, Fragrance(Parfum)

INDICATIONS AND USAGE

1.Place enough product .on hands to cover all surfaces.Rub hands together until dry.
2.Superise children under 6 years of age when using this product to avoid swallowing.

ACTIVE INGREDIENT

Ethyl Alcohol

keep out of reach of children

PURPOSE

Disinfection
Sterilization
No Rinseing

WARNINGS

For external use only. Flammable. Keep away from heat or flame